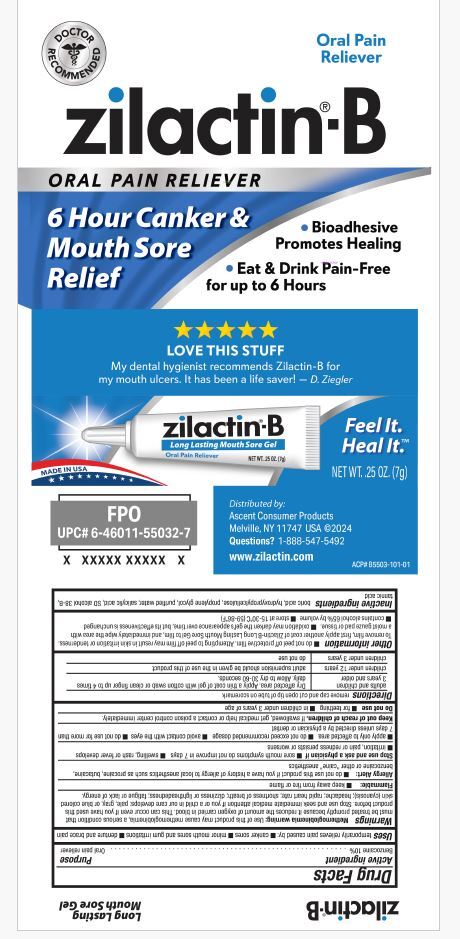 DRUG LABEL: Zilactin-B
NDC: 42829-550 | Form: GEL
Manufacturer: ASCENT CONSUMER PRODUCTS, INC
Category: otc | Type: HUMAN OTC DRUG LABEL
Date: 20251106

ACTIVE INGREDIENTS: BENZOCAINE 0.1 g/1 g
INACTIVE INGREDIENTS: BORIC ACID; HYDROXYPROPYL CELLULOSE (TYPE M); PROPYLENE GLYCOL; SALICYLIC ACID; ALCOHOL; PEPPERMINT OIL; TANNIC ACID; WATER

Zilactin B

Drug Facts

Active ingredient

Benzocaine 10%

Purpose

Oral pain reliever

Use

temporarily relieves pain caused by:

- canker sores
- minor mouth sores and gum irritations
- denture and brace pain

Warnings

Flammable:

- keep away from fire or flame

Allergy Alert:

- do not use this product if you have a history of allergy to local anesthetics such as procaine, butacaine, benzocaine or other “caine” anesthetics

Stop use and ask a physician if

- sore mouth symptoms do not improve in 7 days
- swelling, rash or fever develops
- irritation, pain or redness persists or worsens
- apply only to affected area
- do not exceed recommended dosage
- avoid contact with the eyes
- do not use for more than 7 days unless directed by a physician or dentist

Keep out of reach of children. If swallowed, get medical help or contact a poison control center immediately.

Directions

adults and children 2 years and older | Dry affected area. Apply a thin coat of gel with cotton swab or clean finger up to 4 times daily. Allow to dry 30-60 seconds.
children under 12 years | adult supervision should be given in the use of this product
children under 2 years | do not use, consult a physician or dentist

Other information

- do not peel off protective film. Attempting to peel off film may result in skin irritation or tenderness. To remove film, first apply another coat of Zilactin-B Long Lasting Mouth Sore Gel to film, and immediately wipe the area with a moist gauze pad or tissue.
- contains alcohol 65% by volume
- store at 15-30°C (59-86°F)

Inactive ingredients

Boric acid, hydroxypropylcellulose, propylene glycol, purified water, salicylic acid, SD alcohol 38-B, tannic acid

QUESTIONS

Call 1-888-547-5492

Distributed by Ascent Consumer Products